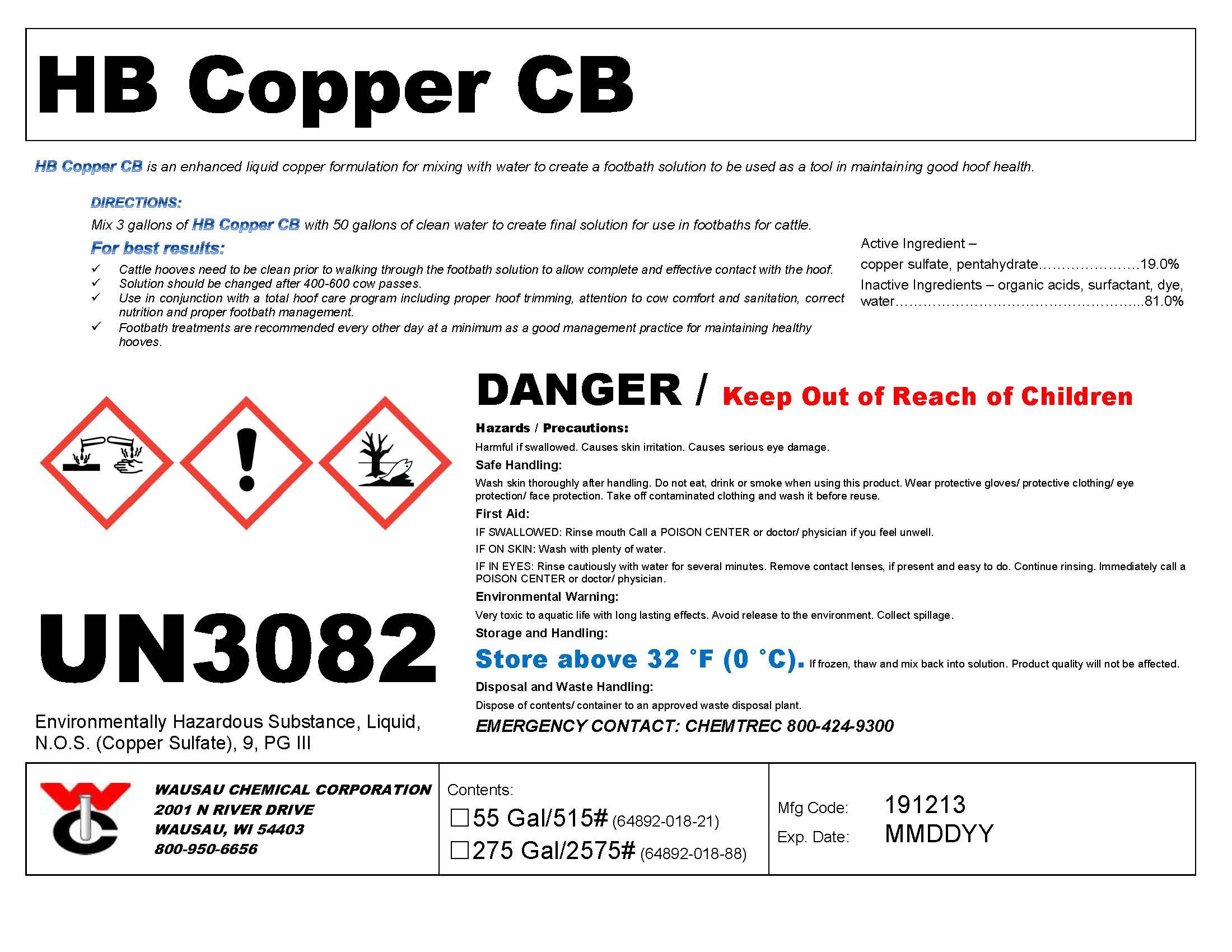 DRUG LABEL: HB Copper CB
NDC: 64892-018 | Form: SOLUTION
Manufacturer: Wausau Chemical
Category: animal | Type: OTC ANIMAL DRUG LABEL
Date: 20191213

ACTIVE INGREDIENTS: CUPRIC SULFATE, BASIC COPPER SULFATE DIBASIC 215.5 g/1 L

HB Copper CB
Liquid Copper Hoof Bath Solution

DISPOSAL AND WASTE HANDLING

Dispose of contents/container to an approved waste disposal plant.

ENVIRONMENTAL WARNING

Very toxic to aquatic life with long lasting effects. Avoid release to the environment. Collect spillage.

GENERAL PRECAUTIONS

DANGER / Keep Out of Reach of Children

First Aid:

IF SWALLOWED: Rinse mouth. Call a POISON CENTER or doctor/ physician if you feel unwell.
IF ON SKIN (or hair): Wash with plenty of water.
IF IN EYES: Rinse cautiously with water for several minutes. Remove contact lenses, if present and easy to do. Continue rinsing.

SAFE HANDLING WARNING

Wash skin thoroughly after handling. Do not eat, drink or smoke when using this product. Wear protective gloves/ protective clothing/ eye protection/ face protection. Take off contaminated clothing and wash it before reuse.

STORAGE AND HANDLING

Store above 32 °F (0 °C). If frozen, thaw and mix back into solution. Product quality will not be affected.

DIRECTIONS:
Mix 3 gallons of HB Copper CB with 50 gallons of clean water to create final solution for use in footbaths for cattle.

For best results:
Cattle hooves need to be clean prior to walking through the footbath solution to allow complete and effective contact with the hoof.
Solution should be changed after 400-600 cow passes.
Use in conjunction with a total hoof care program including proper hoof trimming, attention to cow comfort and sanitation, correct nutrition and proper footbath management.
Footbath treatments are recommended every other day at a minimum as a good management practice for maintaining healthy hooves.

Active Ingredient – copper sulfate, pentahydrate................................................................19.0%
Inactive Ingredients – organic acids, surfactant, dye, water................................................81.0%

Wausau Chemical Corporation

2001 N River Drive

Wausau, WI 54403

800-950-6656